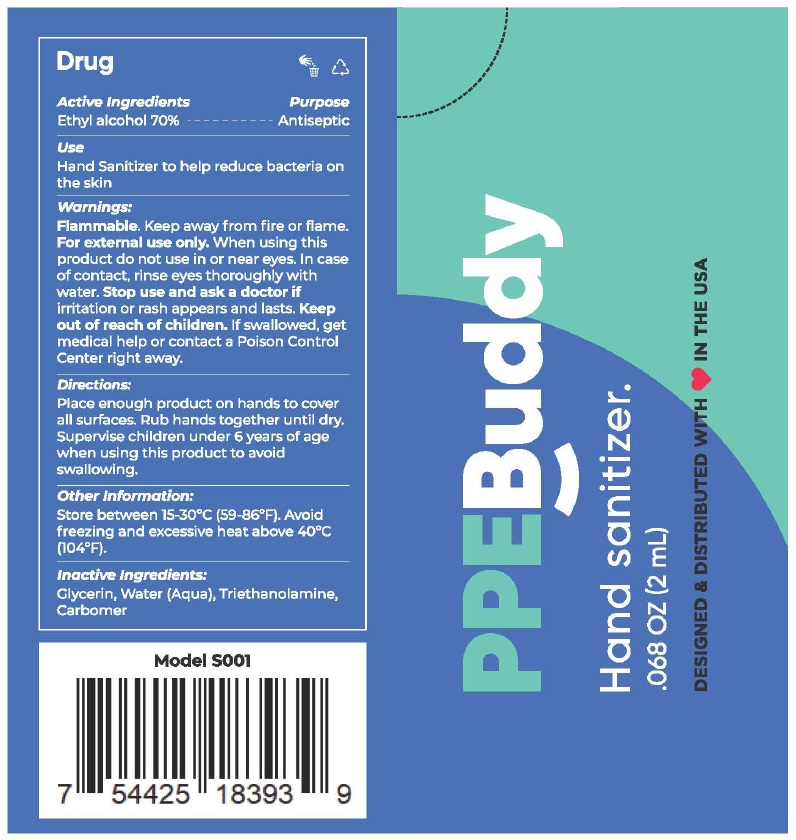 DRUG LABEL: PPE BUDDY
NDC: 80014-001 | Form: GEL
Manufacturer: Tecnología en Sachets, S.A. de C.V.
Category: otc | Type: HUMAN OTC DRUG LABEL
Date: 20200814

ACTIVE INGREDIENTS: ALCOHOL 70 mL/100 mL
INACTIVE INGREDIENTS: WATER; GLYCERIN; TROLAMINE; CARBOMER HOMOPOLYMER, UNSPECIFIED TYPE

Active lngredient

Ethyl alcohol 70%

Purpose

Antiseptic

Use

Hand sanitizer to help reduce bacteria on the skin.

Warnings

Flammable. Keep away from heat or flame

For external use only.

When using this product do not use in or near eyes. In case of contact with eyes, rinse eyes thoroughly with water.

Stop use and ask a doctor if irritation or rash appears & last.

Keep out of reach of children. If swallowed, get medical help or contact a Poison Control Center right away.

Directions

Place enough product on hands to cover all surfaces. Rub hands together until dry.
Supervise children under 6 years of age when using this product to avoid swallowing

Other information

Store between 15-30°C (59-86F)

Avoid freezing and excessive heat above 40°C (104F)

Inactive ingredients

Glycerin, water (Aqua), Triethanolamine, carbomer